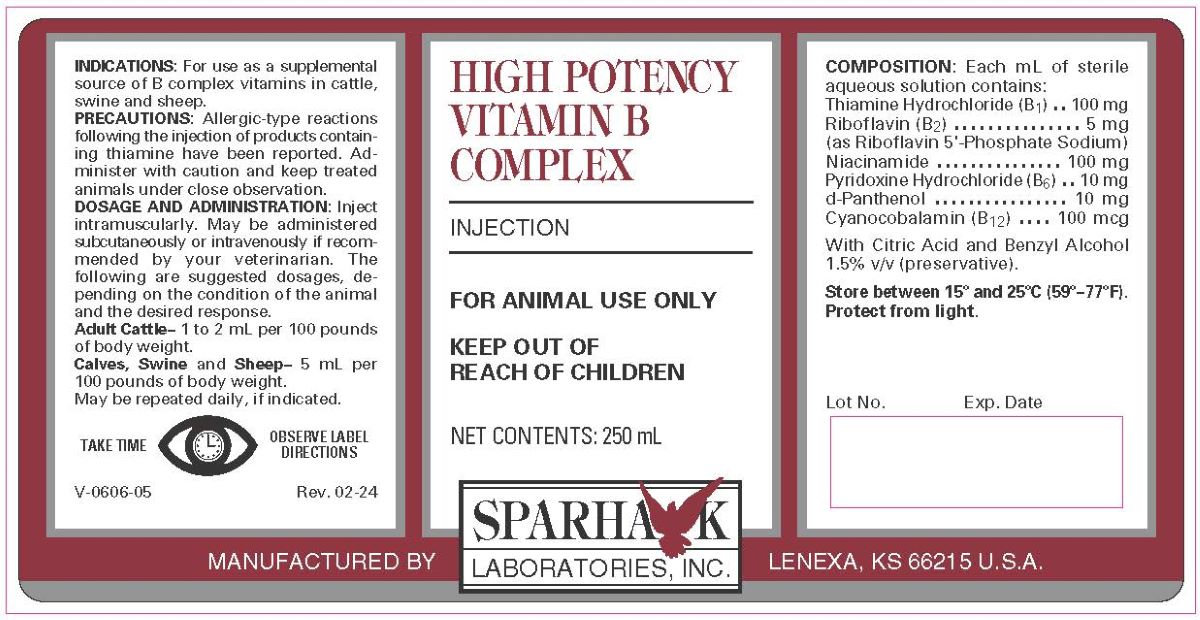 DRUG LABEL: HIGH POTENCY MULTI B COMPLEX
NDC: 58005-606 | Form: INJECTION
Manufacturer: Sparhawk Laboratories, Inc.
Category: animal | Type: OTC ANIMAL DRUG LABEL
Date: 20250409

ACTIVE INGREDIENTS: CYANOCOBALAMIN 0.1 mg/1 mL; THIAMINE HYDROCHLORIDE 100 mg/1 mL; PYRIDOXINE HYDROCHLORIDE 10 mg/1 mL; NIACINAMIDE 100 mg/1 mL; DEXPANTHENOL 10 mg/1 mL; RIBOFLAVIN 5'-PHOSPHATE SODIUM 5 mg/1 mL

HIGH POTENCY VITAMIN B COMPLEX

INDICATIONS

For use as a supplement source of B complex vitamins in cattle, swine and sheep.

PRECAUTIONS

Allergic-type reactions following the injection of products containing thiamine have been reported. Administer with caution and keep treated animals under close observation.

DOSAGE AND ADMINISTRATION

Inject intramuscularly. May be administered subcutaneously or intravenously if recommended by your veterinarian. The following are suggested dosages, depending on the condition of the animal and the desired response.

Adult Cattle--1 to 2 mL per 100 pounds body weight.
Calves, Swine and Sheep--5 mL per 100 pounds of body weight.

May be repeated daily, if indicated.

TAKE TIME OBSERVE LABEL DIRECTIONS

COMPOSITION

Each mL of sterile aqueous solution contains:

Thiamine Hydrochloride (B1) . . . . . . . . . . . . . 100 mg
Riboflavin (B2) . . . . . . . . . . . . . . . . . . . . . . . . .5 mg
(as Riboflavin 5'--Phosphate Sodium)
Niacinamide . . . . . . . . . . . . . . . . . . . . . . . . .100 mg
Pyridoxine Hydrochloride (B6) . . . . . . . . . . . . . 10 mg
d-Panthenol . . . . . . . . . . . . . . . . . . . . . . . . . .10 mg
Cyanocobalamin (B12) . . . . . . . . . . . . . . . . .100 mcg
With Citric Acid and Benzyl Alcohol 1.5% v/v (preservative)

STORAGE AND HANDLING

Store at controlled room temperature between 15o and 30oC (59o-86oF)

Protect from light